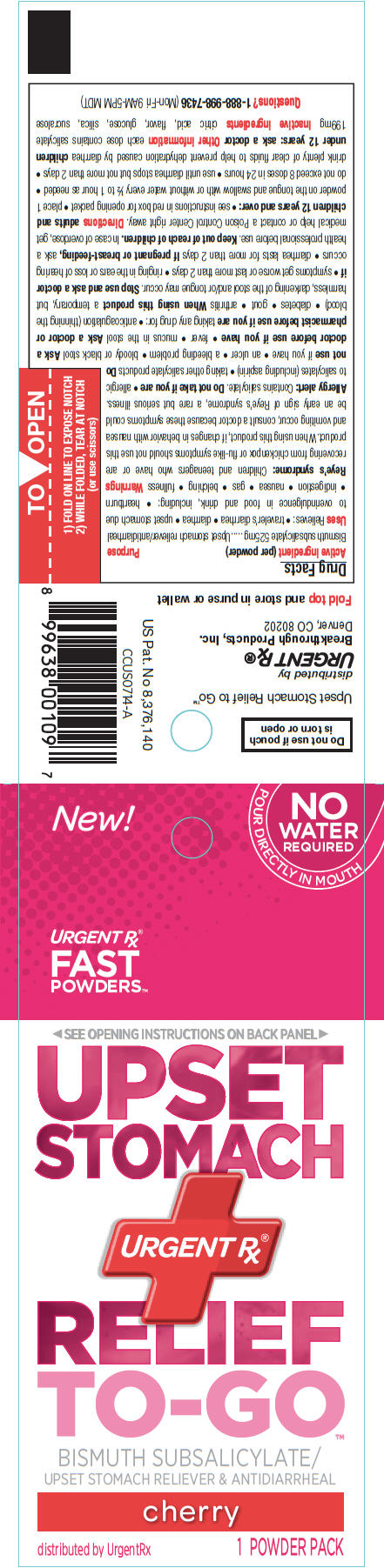 DRUG LABEL: Upset Stomach Relief to Go
NDC: 51596-004 | Form: POWDER
Manufacturer: Breakthrough Products Inc.
Category: otc | Type: HUMAN OTC DRUG LABEL
Date: 20141008

ACTIVE INGREDIENTS: Bismuth subsalicylate 525 mg/1 1
INACTIVE INGREDIENTS: anhydrous citric acid; dextrose; silicon dioxide; sucralose

Upset Stomach Relief to Go™

Drug Facts

Active ingredient (per powder)

Bismuth subsalicylate 525mg

Purpose

Upset stomach reliever/antidiarrheal

Uses

Relieves:

- traveler's diarrhea
- diarrhea
- upset stomach due to overindulgence in food and drink, including:
  - heartburn
  - indigestion
  - nausea
  - gas
  - belching
  - fullness

Warnings

Reye's syndrome

Children and teenagers who have or are recovering from chickenpox or flu-like symptoms should not use this product. When using this product, if changes in behavior with nausea and vomiting occur, consult a doctor because these symptoms could be an early sign of Reye's syndrome, a rare but serious illness.

Allergy alert

Contains salicylate.

Do not take if you are

- allergic to salicylates (including aspirin)
- taking other salicylate products

Do not use if you have

- an ulcer
- a bleeding problem
- bloody or black stool

Ask a doctor before use if you have

- fever
- mucus in the stool

Ask a doctor or pharmacist before use if you are taking any drug for:

- anticoagulation (thinning the blood)
- diabetes
- gout
- arthritis

When using this product a temporary, but harmless, darkening of the stool and/or tongue may occur.

Stop use and ask a doctor if

- symptoms get worse or last more than 2 days
- ringing in the ears or loss of hearing occurs
- diarrhea lasts for more than 2 days

PREGNANCY OR BREAST FEEDING

If pregnant or breast-feeding, ask a health professional before use.

Keep out of reach of children. In case of overdose, get medical help or contact a Poison Control Center right away.

Directions

adults and children 12 years and over:

- see instructions in red box for opening packet
- place 1 powder on the tongue and swallow with or without water every ½ to 1 hour as needed
- do not exceed 8 doses in 24 hours
- use until diarrhea stops but not more than 2 days
- drink plenty of clear fluids to help prevent dehydration caused by diarrhea

children under 12 years: ask a doctor

Other information

each dose contains salicylate 199mg

Inactive ingredients

citric acid, flavor, glucose, silica, sucralose

Questions?

1-888-998-7436 (Mon-Fri 9AM-5PM MDT)

Do not use if pouch
is torn or open

distributed by
URGENT Rx®
Breakthrough Products, Inc.
Denver, CO 80202

PRINCIPAL DISPLAY PANEL - 1 Powder Packet

New!

NO
WATER
REQUIRED
POUR DIRECTLY IN MOUTH

URGENT Rx®
FAST
POWDERS™

◀ SEE OPENING INSTRUCTIONS ON BACK PANEL ▶

UPSET
STOMACH

URGENT Rx®

RELIEF
TO-GO™

BISMUTH SUBSALICYLATE/
UPSET STOMACH RELIEVER & ANTIDIARRHEAL

cherry

distributed by UrgentRx
1 POWDER PACK